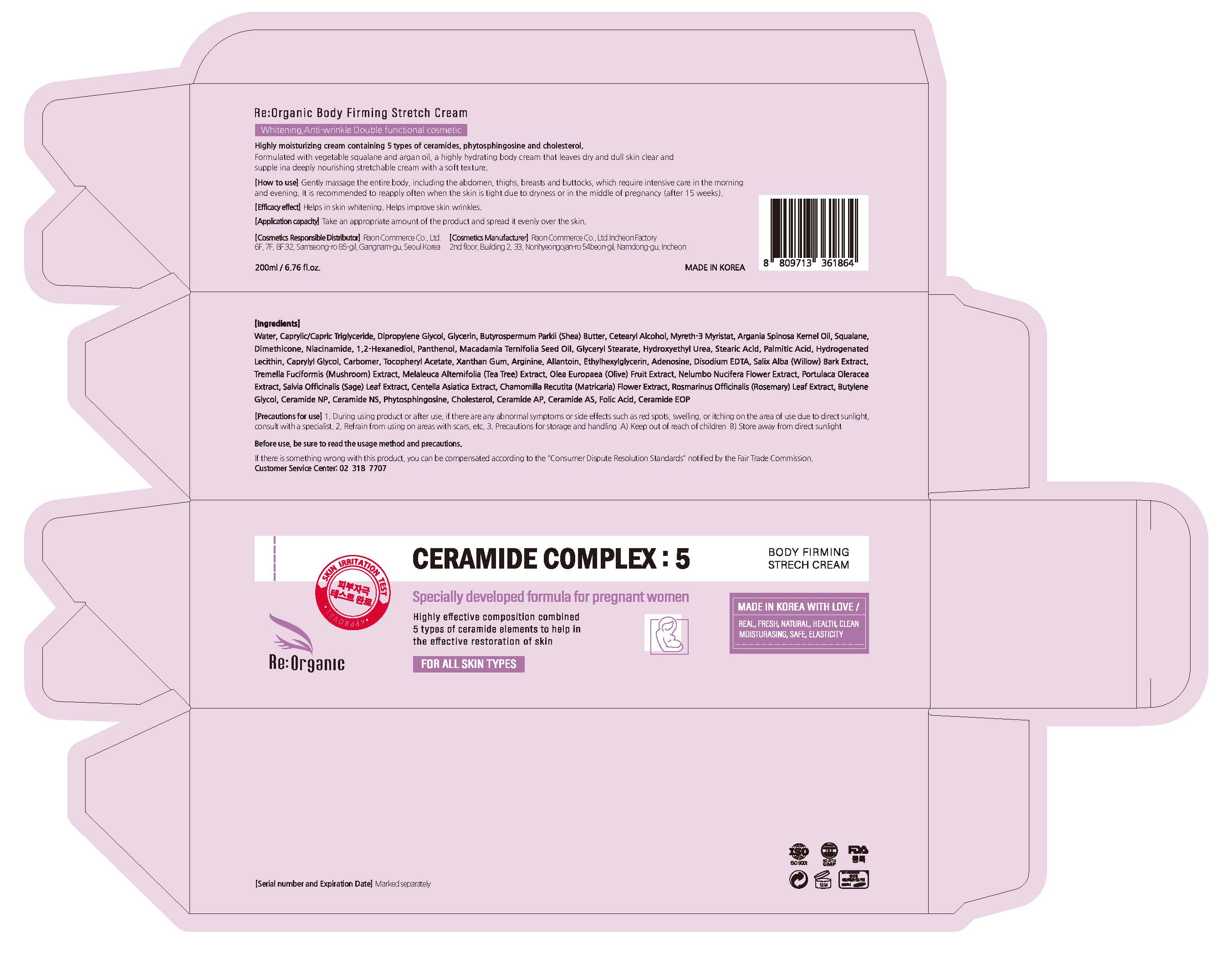 DRUG LABEL: Reoganic Body Firming StretchCream
NDC: 82083-0026 | Form: CREAM
Manufacturer: LAON COMMERCE co ltd
Category: otc | Type: HUMAN OTC DRUG LABEL
Date: 20230922

ACTIVE INGREDIENTS: ADENOSINE 0.04 g/100 mL; NIACINAMIDE 2 g/100 mL
INACTIVE INGREDIENTS: WATER; SHEA BUTTER

ACTIVE INGREDIENT

Niacinamide, Adenosine

INACTIVE INGREDIENT

Water
Caprylic/Capric Triglyceride
Dipropylene Glycol
Glycerin
Butyrospermum Parkii (Shea) Butter
Cetearyl Alcohol
Myreth-3 Myristat
Argania Spinosa Kernel Oil
Squalane
Dimethicone
1,2-Hexanediol
Panthenol
Macadamia Ternifolia Seed Oil
Glyceryl Stearate
Hydroxyethyl Urea
Stearic Acid
Palmitic Acid
Hydrogenated Lecithin
Caprylyl Glycol
Carbomer
Tocopheryl Acetate
Xanthan Gum
Arginine
Allantoin
Ethylhexylglycerin
Disodium EDTA
Salix Alba (Willow) Bark Extract
Tremella Fuciformis (Mushroom) Extract
Melaleuca Alternifolia (Tea Tree) Extract
Olea Europaea (Olive) Fruit Extract
Nelumbo Nucifera Flower Extract
Portulaca Oleracea Extract
Salvia Officinalis (Sage) Leaf Extract
Centella Asiatica Extract
Chamomilla Recutita (Matricaria) Flower Extract
Rosmarinus Officinalis (Rosemary) Leaf Extract
Butylene Glycol
Ceramide NP
Ceramide NS
Phytosphingosine
Cholesterol
Ceramide AP
Ceramide AS
Folic Acid
Ceramide EOP

PURPOSE

skin protect

KEEP OUT OF REACH OF THE CHILDREN

INDICATIONS AND USAGE

Gently massage the entire body, including the abdomen, thighs, breasts and buttocks, which require intensive care in the morning and evening. It is recommended to reapply often when the skin is tight due to dryness or in the middle of pregnancy (after 15 weeks).

WARNINGS

(Precautions for use)

1. During using product or after use, if there are any abnormal symptoms or side effects such as red spots, swelling or itching in the area of use due to direct sunlight, consult with a specialist.

2. Refrain from using on areas with scars, etc.

3. Precautions for storage and handling

A) Keep out of reach of children

B) Store away from direct sunlight

DOSAGE AND ADMINISTRATION

topical use only